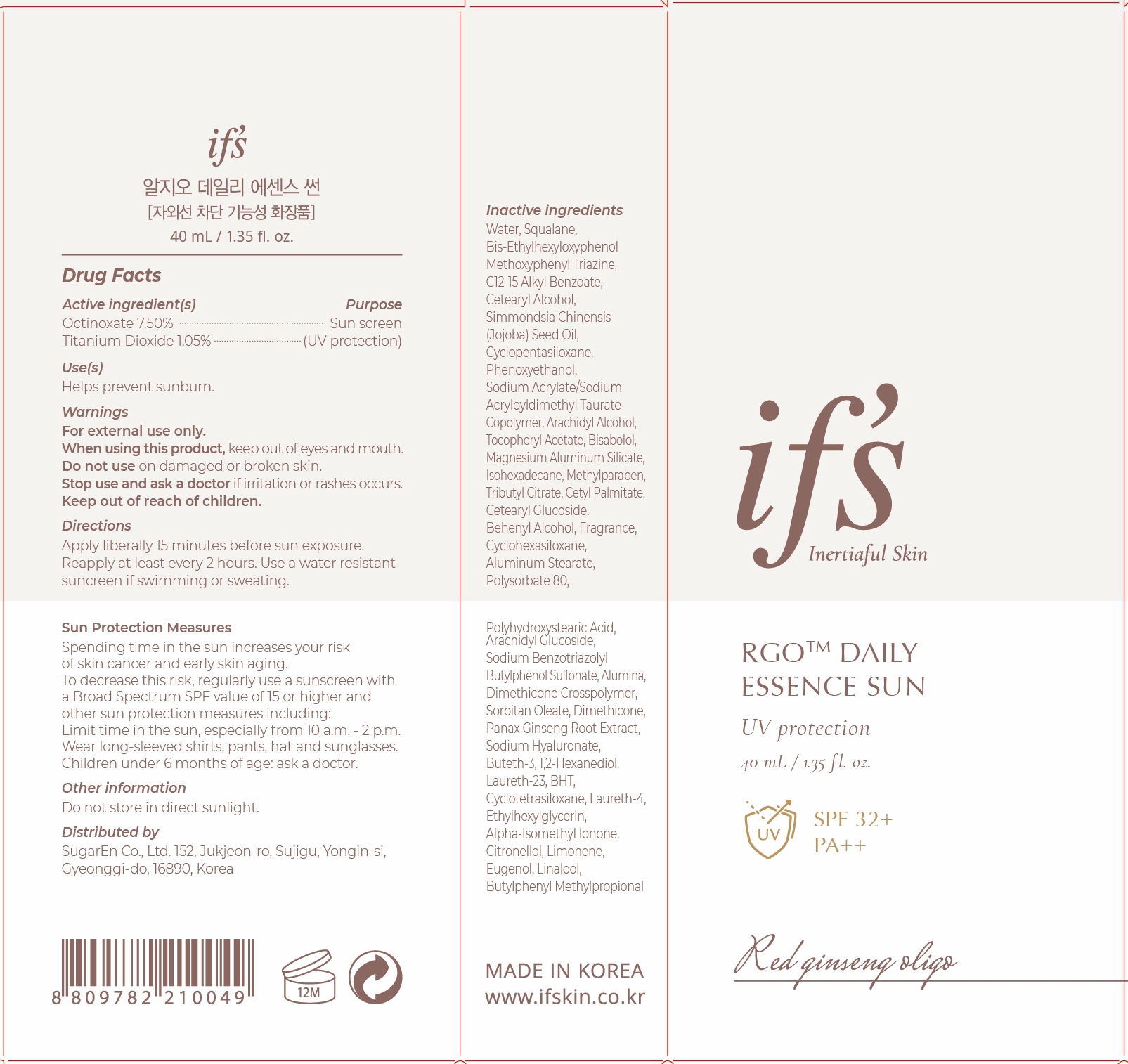 DRUG LABEL: RGO DAILY ESSENCE SUN
NDC: 81897-501 | Form: CREAM
Manufacturer: SugarEn Co., Ltd.
Category: otc | Type: HUMAN OTC DRUG LABEL
Date: 20210528

ACTIVE INGREDIENTS: TITANIUM DIOXIDE 1.05 g/100 mL; OCTINOXATE 7.5 g/100 mL
INACTIVE INGREDIENTS: WATER; PHENOXYETHANOL; LEVOMENOL; BUTETH-3; 1,2-HEXANEDIOL; LAURETH-23; BUTYLATED HYDROXYTOLUENE; EUGENOL; LINALOOL, (+/-)-; BUTYLPHENYL METHYLPROPIONAL; JOJOBA OIL; ETHYLHEXYLGLYCERIN; ISOMETHYL-.ALPHA.-IONONE; BEMOTRIZINOL; ALKYL (C12-15) BENZOATE; CETOSTEARYL ALCOHOL; SODIUM ACRYLATE/SODIUM ACRYLOYLDIMETHYLTAURATE COPOLYMER (4000000 MW); .ALPHA.-TOCOPHEROL ACETATE; ARACHIDYL GLUCOSIDE; ASIAN GINSENG; HYALURONATE SODIUM; LIMONENE, (+)-; ARACHIDYL ALCOHOL; MAGNESIUM ALUMINUM SILICATE; ISOHEXADECANE; METHYLPARABEN; CETYL PALMITATE; SODIUM BENZOTRIAZOLYL BUTYLPHENOL SULFONATE; DIMETHICONE; CYCLOMETHICONE 4; LAURETH-4; CYCLOMETHICONE 5; TRIBUTYL CITRATE; CETEARYL GLUCOSIDE; DOCOSANOL; CYCLOMETHICONE 6; ALUMINUM STEARATE; POLYSORBATE 80; ALUMINUM OXIDE; SORBITAN MONOOLEATE; .BETA.-CITRONELLOL, (R)-; SQUALANE

81897-501 RGO DAILY ESSENCE SUN

Active ingredient(s)

Octinoxate 7.5%

Titanium Dioxide 1.05%

Purpose

Sun screen(UV protection)

Use(s)

Helps prevent sunburn.

Warnings

For external only.

Spending time in the sun increases your risk of skin cancer and early skin aging. To decrease this risk, regularly use a sunscreen with a Broad Spectrum SPF value of 15 or higher and other sun protection measures including:

Limit time in the sun, especially from 10 a.m. - 2 p.m.

Wear long-sleeved shrits, pants, hat and sunglasses.

Children under 6 months of age: ask a doctor.

When using this product

keep out of eyes and mouth.

Do not use

on damaged or broken skin.

Stop use and ask a doctor

if irritation or rashes occurs.

Keep out of reach of children

Other Information

Do not store in direct sunlight.

Directions

Apply liberally 15 minutes before sun exposure.

reapply at least every 2 hours.

Use a water resistant suncreen if swimming or sweating.

Inactive indredients

Water, Squalane, Bis-Ethylhexyloxyphenol Methoxyphenyl Triazine, C12-15 Alkyl Benzoate, Cetearyl Alcohol, Simmondsia Chinensis (Jojoba) Seed Oil, Cyclopentasiloxane, Phenoxyethanol, Sodium Acrylate/Sodium Acryloyldimethyl Taurate Copolymer, Arachidyl Alcohol, Tocopheryl Acetate, Bisabolol, Magnesium Aluminum Silicate, Isohexadecane, Methylparaben, Tributyl Citrate, Cetyl Palmitate, Cetearyl Glucoside, Behenyl Alcohol, Fragrance, Cyclohexasiloxane, Aluminum Stearate, Polysorbate 80, Polyhydroxystearic Acid, Arachidyl Glucoside, Sodium Benzotriazolyl Butylphenol Sulfonate, Alumina, Dimethicone Crosspolymer, Sorbitan Oleate, Dimethicone, Panax Ginseng Root Extract, Sodium Hyaluronate, Buteth-3, 1,2-Hexanediol, Laureth-23, BHT, Cyclotetrasiloxane, Laureth-4, Ethylhexylglycerin, Alpha-Isomethyl Ionone, Citronellol, Limonene, Eugenol, Linalool, Butylphenyl Methylpropional